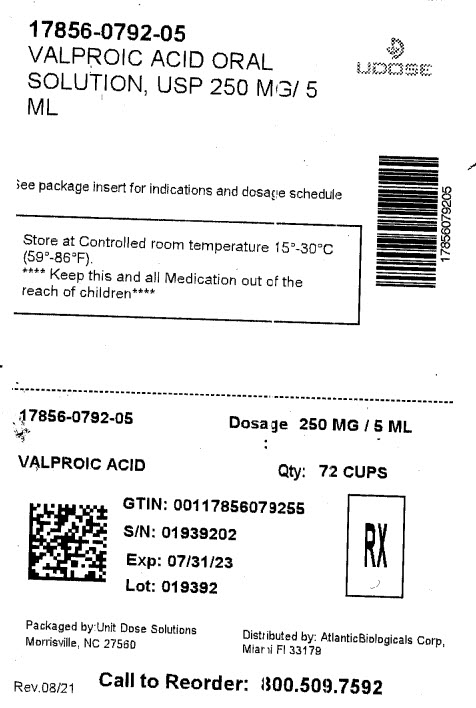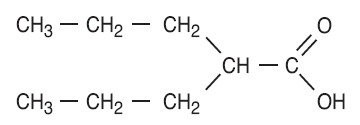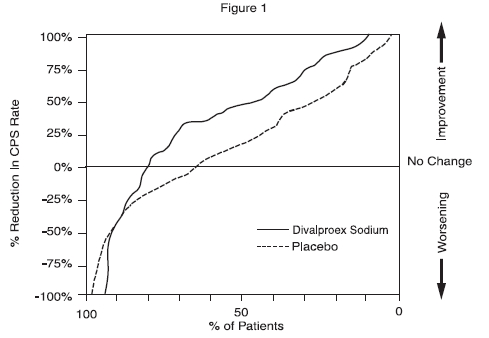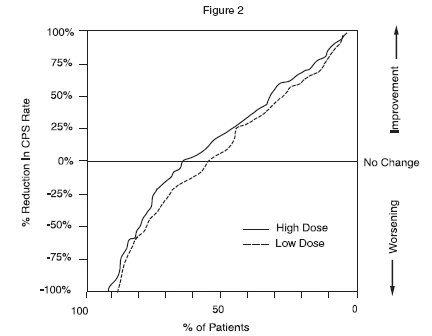 DRUG LABEL: Valproic Acid
NDC: 17856-0792 | Form: SOLUTION
Manufacturer: ATLANTIC BIOLOGICALS CORP.
Category: prescription | Type: HUMAN PRESCRIPTION DRUG LABEL
Date: 20240516

ACTIVE INGREDIENTS: VALPROIC ACID 250 mg/5 mL
INACTIVE INGREDIENTS: FD&C RED NO. 40; METHYLPARABEN; RASPBERRY; PROPYLPARABEN; WATER; SODIUM HYDROXIDE; SORBITOL; SUCROSE

Valproic Acid Oral Solution, USP

Rx Only

BOXED WARNING

BOXED WARNING

HEPATOTOXICITY

HEPATIC FAILURE RESULTING IN FATALITIES HAS OCCURRED IN PATIENTS RECEIVING VALPROIC ACID. EXPERIENCE HAS INDICATED THAT CHILDREN UNDER THE AGE OF TWO YEARS ARE AT A CONSIDERABLY INCREASED RISK OF DEVELOPING FATAL HEPATOTOXICITY, ESPECIALLY THOSE ON MULTIPLE ANTICONVULSANTS, THOSE WITH CONGENITAL METABOLIC DISORDERS, THOSE WITH SEVERE SEIZURE DISORDERS ACCOMPANIED BY MENTAL RETARDATION, AND THOSE WITH ORGANIC BRAIN DISEASE. WHEN VALPROIC ACID PRODUCTS ARE USED IN THIS PATIENT GROUP, THEY SHOULD BE USED WITH EXTREME CAUTION AND AS A SOLE AGENT. THE BENEFITS OF THERAPY SHOULD BE WEIGHED AGAINST THE RISKS. ABOVE THIS AGE GROUP, EXPERIENCE IN EPILEPSY HAS INCIDENCE THAT THE INCIDENT OF FATAL HEPATOTOXICITY DECREASES CONSIDERABLY IN PROGRESSIVELY OLDER PATIENT GROUPS.

THESE INCIDENTS USUALLY HAVE OCCURRED DURING THE FIRST SIX MONTHS OF TREATMENT. SERIOUS OR FATAL HEPATOTOXICITY MAY BE PRECEDED BY NON-SPECIFIC SYMPTOMS SUCH AS MALAISE, WEAKNESS, LETHARGY, FACIAL EDEMA, ANOREXIA AND VOMITING. IN PATIENTS WITH EPILEPSY, A LOSS OF SEIZURE CONTROL MAY ALSO OCCUR. PATIENTS SHOULD BE MONITORED CLOSELY FOR APPEARANCE OF THESE SYMPTOMS. LIVER FUNCTION TESTS SHOULD BE PERFORMED PRIOR TO THERAPY AND AT FREQUENT INTERVALS THEREAFTER, ESPECIALLY DURING THE FIRST SIX MONTHS.

TERATOGENICITY

VALPROATE CAN PRODUCE TERATOGENIC EFFECTS SUCH AS NEURAL TUBE DEFECTS (E.G., SPINA BIFIDA). ACCORDINGLY, THE USE OF VALPROATE PRODUCTS IN WOMEN OF CHILDBEARING POTENTIAL REQUIRES THAT THE BENEFITS OF ITS USE BE WEIGHED AGAINST THE RISK OF INJURY TO THE FETUS.

THIS IS ESPECIALLY IMPORTANT WHEN THE TREATMENT OF A SPONTANEOUSLY REVERSIBLE CONDITION NOT ORDINARILY ASSOCIATED WITH PERMANENT INJURY OR RISK OF DEATH (E.G., MIGRAINE) IS CONTEMPLATED. SEE WARNINGS, INFORMATION FOR PATIENTS.

A PATIENT INFORMATION LEAFLET DESCRIBING THE TERATOGENIC POTENTIAL OF VALPROATE IS AVAILABLE FOR PATIENTS.

PANCREATITIS

CASES OF LIFE-THREATENING PANCREATITIS HAVE BEEN REPORTED IN BOTH CHILDREN AND ADULTS RECEIVING VALPROATE. SOME OF THE CASES HAVE BEEN DESCRIBED AS HEMORRHAGIC WITH A RAPID PROGRESSION FROM INITIAL SYMPTOMS TO DEATH. CASES HAVE BEEN REPORTED SHORTLY AFTER INITIAL USE AS WELL AS AFTER SEVERAL YEARS OF USE. PATIENTS AND GUARDIANS SHOULD BE WARNED THAT ABDOMINAL PAIN, NAUSEA, VOMITING, AND/OR ANOREXIA CAN BE SYMPTOMS OF PANCREATITIS THAT REQUIRE PROMPT MEDICAL EVALUATION. IF PANCREATITIS IS DIAGNOSED, VALPROATE SHOULD ORDINARILY BE DISCONTINUED. ALTERNATIVE TREATMENT FOR THE UNDERLYING MEDICAL CONDITION SHOULD BE INITIATED AS CLINICALLY INDICATED. (See and .) WARNINGSPRECAUTIONS

DESCRIPTION

Valproic acid is a carboxylic acid designated as 2-propylpentanoic acid. It is also known as dipropylacetic acid. Valproic acid has the following structure:

Valproic acid (pKa 4.8) has a molecular weight of 144 and occurs as a colorless liquid with a characteristic odor. It is slightly soluble in water (1.3 mg/mL) and very soluble in organic solvents.

Valproic acid oral solution, USP is an antiepileptic for oral administration. The oral solution contains the equivalent of 250 mg valproic acid per 5 mL as the sodium salt.

FD&C Red No. 40, methylparaben, natural and artificial raspberry flavor, propylparaben, purified water, sodium hydroxide, sorbitol, and sucrose. Inactive Ingredients:

CLINICAL PHARMACOLOGY

Pharmacodynamics

Valproic acid dissociates to the valproate ion in the gastrointestinal tract. The mechanisms by which valproate exerts its antiepileptic effects have not been established. It has been suggested that its activity in epilepsy is related to increased brain concentrations of gamma-aminobutyric acid (GABA).

Pharmacokinetics

Absorption/Bioavailability

Equivalent oral doses of divalproex sodium products and valproic acid capsules deliver equivalent quantities of valproate ion systemically. Although the rate of valproate ion absorption may vary with the formulation administered (liquid, solid, or sprinkle), conditions of use (e.g., fasting or postprandial) and the method of administration (e.g., whether the contents of the capsule are sprinkled on food or the capsule is taken intact), these differences should be of minor clinical importance under the steady state conditions achieved in chronic use in the treatment of epilepsy.

However, it is possible that differences among the various valproate products in Tmax and Cmax could be important upon initiation of treatment. For example, in single dose studies, the effect of feeding had a greater influence on the rate of absorption of the divalproex sodium tablet (increase in Tmax from 4 to 8 hours) than on the absorption of the divalproex sodium sprinkle capsules (increase in Tmax from 3.3 to 4.8 hours).

While the absorption rate from the G.I. tract and fluctuation in valproate plasma concentrations vary with dosing regimen and formulation, the efficacy of valproate as an anticonvulsant in chronic use is unlikely to be affected. Experience employing dosing regimens from once-a-day to four-times-a-day, as well as studies in primate epilepsy models involving constant rate infusion, indicate that total daily systemic bioavailability (extent of absorption) is the primary determinant of seizure control and that differences in the ratios of plasma peak to trough concentrations between valproate formulations are inconsequential from a practical clinical standpoint.

Co-administration of oral valproate products with food and substitution among the various divalproex sodium and valproic acid formulations should cause no clinical problems in the management of patients with epilepsy (see). Nonetheless, any changes in dosage administration, or the addition or discontinuance of concomitant drugs should ordinarily be accompanied by close monitoring of clinical status and valproate plasma concentrations. DOSAGE AND ADMINISTRATION

Distribution:

Protein Binding:

The plasma protein binding of valproate is concentration dependent and the free fraction increases from approximately 10% at 40 μg/mL to 18.5% at 130 μg/mL. Protein binding of valproate is reduced in the elderly, in patients with chronic hepatic diseases, in patients with renal impairment, and in the presence of other drugs (e.g., aspirin). Conversely, valproate may displace certain protein-bound drugs (e.g., phenytoin, carbamazepine, warfarin, and tolbutamide). (See for more detailed information on the pharmacokinetic interactions of valproate with other drugs.) PRECAUTIONS, Drug Interactions

CNS Distribution

Valproate concentrations in cerebrospinal fluid (CSF) approximate unbound concentrations in plasma (about 10% of total concentration).

Metabolism

Valproate is metabolized almost entirely by the liver. In adult patients on monotherapy, 30-50% of an administered dose appears in urine as a glucuronide conjugate. Mitochondrial ß-oxidation is the other major metabolic pathway, typically accounting for over 40% of the dose. Usually, less than 15-20% of the dose is eliminated by other oxidative mechanisms. Less than 3% of an administered dose is excreted unchanged in urine.

The relationship between dose and total valproate concentration is nonlinear; concentration does not increase proportionally with the dose, but rather, increases to a lesser extent due to saturable plasma protein binding. The kinetics of unbound drug are linear.

Elimination

Mean plasma clearance and volume of distribution for total valproate are 0.56 L/hr/1.73 m and 11 L/1.73 m , respectively. Mean plasma clearance and volume of distribution for free valproate are 4.6 L/hr/1.73 m and 92 L/1.73 m . Mean terminal half-life for valproate monotherapy ranged from 9 to 16 hours following oral dosing regimens of 250 to 1000 mg.^2^2^2^2

The estimates cited apply primarily to patients who are not taking drugs that affect hepatic metabolizing enzyme systems. For example, patients taking enzyme-inducing antiepileptic drugs (carbamazepine, phenytoin, and phenobarbital) will clear valproate more rapidly. Because of these changes in valproate clearance, monitoring of antiepileptic concentrations should be intensified whenever concomitant antiepileptics are introduced or withdrawn.

Special Populations

Effect of Age:

Neonates

Children within the first two months of life have a markedly decreased ability to eliminate valproate compared to older children and adults. This is a result of reduced clearance (perhaps due to delay in development of glucuronosyltransferase and other enzyme systems involved in valproate elimination) as well as increased volume of distribution (in part due to decreased plasma protein binding). For example, in one study, the half-life in children under 10 days ranged from 10 to 67 hours compared to a range of 7 to 13 hours in children greater than 2 months.

Children

Pediatric patients (i.e., between 3 months and 10 years) have 50% higher clearances expressed on weight (i.e., mL/min/kg) than do adults. Over the age of 10 years, children have pharmacokinetic parameters that approximate those of adults.

Elderly

The capacity of elderly patients (age range: 68 to 89 years) to eliminate valproate has been shown to be reduced compared to younger adults (age range: 22 to 26). Intrinsic clearance is reduced by 39%; the free fraction is increased by 44%. Accordingly, the initial dosage should be reduced in the elderly. (See). DOSAGE AND ADMINISTRATION

Effect of Gender

There are no differences in the body surface area adjusted unbound clearance between males and females (4.8 ± 0.17 and 4.7 ± 0.07 L/hr per 1.73 m , respectively).^2

Effect of Race

The effects of race on the kinetics of valproate have not been studied.

Effect of Disease

Liver Disease

(See and). Liver disease impairs the capacity to eliminate valproate. In one study, the clearance of free valproate was decreased by 50% in 7 patients with cirrhosis and by 16% in 4 patients with acute hepatitis, compared with 6 healthy subjects. In that study, the half-life of valproate was increased from 12 to 18 hours. Liver disease is also associated with decreased albumin concentrations and larger unbound fractions (2 to 2.6 fold increase) of valproate. Accordingly, monitoring of total concentrations may be misleading since free concentrations may be substantially elevated in patients with hepatic disease whereas total concentrations may appear to be normal. , , BOXED WARNINGCONTRAINDICATIONSWARNINGS

Renal Disease

A slight reduction (27%) in the unbound clearance of valproate has been reported in patients with renal failure (creatinine clearance < 10 mL/minute); however, hemodialysis typically reduces valproate concentrations by about 20%. Therefore, no dosage adjustment appears to be necessary in patients with renal failure. Protein binding in these patients is substantially reduced; thus, monitoring total concentrations may be misleading.

Plasma Levels and Clinical Effect

The relationship between plasma concentration and clinical response is not well documented. One contributing factor is the nonlinear, concentration dependent protein binding of valproate which affects the clearance of the drug. Thus, monitoring of total serum valproate cannot provide a reliable index of the bioactive valproate species.

For example, because the plasma protein binding of valproate is concentration dependent, the free fraction increases from approximately 10% at 40 μg/mL to 18.5% at 130 μg/mL. Higher than expected free fractions occur in the elderly, in hyperlipidemic patients, and in patients with hepatic and renal diseases.

Epilepsy:

The therapeutic range is commonly considered to be 50 to 100 μg/mL of total valproate, although some patients may be controlled with lower or higher plasma concentrations.

Clinical Trials

The studies described in the following section were conducted using divalproex sodium tablets.

Epilepsy

The efficacy of divalproex sodium in reducing the incidence of complex partial seizures (CPS) that occur in isolation or in association with other seizure types was established in two controlled trials.

In one, multiclinic, placebo controlled study employing an add-on design (adjunctive therapy), 144 patients who continued to suffer eight or more CPS per 8 weeks during an 8 week period of monotherapy with doses of either carbamazepine or phenytoin sufficient to assure plasma concentrations within the "therapeutic range" were randomized to receive, in addition to their original antiepilepsy drug (AED), either divalproex sodium or placebo. Randomized patients were to be followed for a total of 16 weeks. The following table presents the findings.

Adjunctive Therapy Study
Median Incidence of CPS per 8 Weeks
Add-on; Treatment | Number of; Patients | Baseline; Incidence | Experimental; Incidence
Divalproex Sodium | 75 | 16.0 | 8.9* [*Reduction from baseline statistically significantly greater for divalproex sodium than placebo at p ≤ 0.05 level.]
Placebo | 69 | 14.5 | 11.5

Figure 1 presents the proportion of patients (X axis) whose percentage reduction from baseline in complex partial seizure rates was at least as great as that indicated on the Y axis in the adjunctive therapy study. A positive percent reduction indicates an improvement (i.e., a decrease in seizure frequency), while a negative percent reduction indicates worsening. Thus, in a display of this type, the curve for an effective treatment is shifted to the left of the curve for placebo. This figure shows that the proportion of patients achieving any particular level of improvement was consistently higher for divalproex sodium than for placebo. For example, 45% of patients treated with divalproex sodium had a ≥ 50% reduction in complex partial seizure rate compared to 23% of patients treated with placebo.

The second study assessed the capacity of divalproex sodium to reduce the incidence of CPS when administered as the sole AED. The study compared the incidence of CPS among patients randomized to either a high or low dose treatment arm. Patients qualified for entry into the randomized comparison phase of this study only if 1) they continued to experience 2 or more CPS per 4 weeks during an 8 to 12 week long period of monotherapy with adequate doses of an AED (i.e., phenytoin, carbamazepine, phenobarbital, or primidone) and 2) they made a successful transition over a two week interval to divalproex sodium. Patients entering the randomized phase were then brought to their assigned target dose, gradually tapered off their concomitant AED and followed for an interval as long as 22 weeks. Less than 50% of the patients randomized, however, completed the study. In patients converted to divalproex sodium monotherapy, the mean total valproate concentrations during monotherapy were 71 and 123 μg/mL in the low dose and high dose groups, respectively.

The following table presents the findings for all patients randomized who had at least one postrandomization assessment.

Monotherapy Study
Median Incidence of CPS per 8 Weeks
Treatment | Number; of Patients | Baseline; Incidence | Randomized Phase; Incidence
High dose divalproex sodium | 131 | 13.2 | 10.7* [*Reduction from baseline statistically significantly greater for high dose than low dose at p ≤ 0.05 level.]
Low dose divalproex sodium | 134 | 14.2 | 13.8

Figure 2 presents the proportion of patients (X axis) whose percentage reduction from baseline in complex partial seizure rates was at least as great as that indicated on the Y axis in the monotherapy study. A positive percent reduction indicates an improvement (i.e., a decrease in seizure frequency), while a negative percent reduction indicates worsening. Thus, in a display of this type, the curve for a more effective treatment is shifted to the left of the curve for a less effective treatment. This figure shows that the proportion of patients achieving any particular level of reduction was consistently higher for high dose divalproex sodium than for low dose divalproex sodium. For example, when switching from carbamazepine, phenytoin, phenobarbital or primidone monotherapy to high dose divalproex sodium monotherapy, 63% of patients experienced no change or a reduction in complex partial seizure rates compared to 54% of patients receiving low dose divalproex sodium.

INDICATIONS AND USAGE

Valproic acid is indicated as monotherapy and adjunctive therapy in the treatment of patients with complex partial seizures that occur either in isolation or in association with other types of seizures. Valproic acid is indicated for use as sole and adjunctive therapy in the treatment of simple and complex absence seizures, and adjunctively in patients with multiple seizure types which include absence seizures.

Simple absence is defined as very brief clouding of the sensorium or loss of consciousness accompanied by certain generalized epileptic discharges without other detectable clinical signs. Complex absence is the term used when other signs are also present.

SEE FOR STATEMENT REGARDING FATAL HEPATIC DYSFUNCTION. WARNINGS

CONTRAINDICATIONS

VALPROIC ACID SHOULD NOT BE ADMINISTERED TO PATIENTS WITH HEPATIC DISEASE OR SIGNIFICANT HEPATIC DYSFUNCTION.

Valproic acid is contraindicated in patients with known hypersensitivity to the drug.

Valproic acid is contraindicated in patients with known urea cycle disorders (see). WARNINGS

WARNINGS

Hepatotoxicity

Hepatic failure resulting in fatalities has occurred in patients receiving valproic acid. These incidents usually have occurred during the first six months of treatment. Serious or fatal hepatotoxicity may be preceded by non-specific symptoms such as malaise, weakness, lethargy, facial edema, anorexia, and vomiting. In patients with epilepsy, a loss of seizure control may also occur. Patients should be monitored closely for appearance of these symptoms. Liver function tests should be performed prior to therapy and at frequent intervals thereafter, especially during the first six months. However, healthcare providers should not rely totally on serum biochemistry since these tests may not be abnormal in all instances, but should also consider the results of careful interim medical history and physical examination.

Caution should be observed when administering valproic acid to patients with a prior history of hepatic disease. Patients on multiple anticonvulsants, children, those with congenital metabolic disorders, those with severe seizure disorders accompanied by mental retardation, and those with organic brain disease may be at particular risk. Experience has indicated that children under the age of two years are at considerably increased risk of developing fatal hepatotoxicity, especially those with the aforementioned conditions. When valproic acid products are used in this patient group, they should be used with extreme caution and as a sole agent. The benefits of therapy should be weighed against the risks. Above this age group, experience has indicated that the incidence of fatal hepatotoxicity decreases considerably in progressively older patient groups.

The drug should be discontinued immediately in the presence of significant hepatic dysfunction, suspected or apparent. In some cases, hepatic dysfunction has progressed in spite of discontinuation of drug.

Usage in Pregnancy

VALPROATE CAN PRODUCE TERATOGENIC EFFECTS. DATA SUGGEST THAT THERE IS AN INCREASED INCIDENCE OF CONGENITAL MALFORMATIONS ASSOCIATED WITH THE USE OF VALPROATE BY WOMEN WITH SEIZURE DISORDERS DURING PREGNANCY WHEN COMPARED TO THE INCIDENCE IN WOMEN WITH SEIZURE DISORDERS WHO DO NOT USE ANTIEPILEPTIC DRUGS DURING PREGNANCY, THE INCIDENCE IN WOMEN WITH SEIZURE DISORDERS WHO USE OTHER ANTIEPILEPTIC DRUGS, AND THE BACKGROUND INCIDENCE FOR THE GENERAL POPULATION. THEREFORE, VALPROATE SHOULD BE CONSIDERED FOR WOMEN OF CHILDBEARING POTENTIAL ONLY AFTER THE RISKS HAVE BEEN THOROUGHLY DISCUSSED WITH THE PATIENT AND WEIGHED AGAINST THE POTENTIAL BENEFITS OF TREATMENT.

THERE ARE MULTIPLE REPORTS IN THE CLINICAL LITERATURE THAT INDICATE THE USE OF ANTIEPILEPTIC DRUGS DURING PREGNANCY RESULTS IN AN INCREASED INCIDENCE OF CONGENITAL MALFORMATIONS IN OFFSPRING. ANTIEPILEPTIC DRUGS, INCLUDING VALPROATE, SHOULD BE ADMINISTERED TO WOMEN OF CHILDBEARING POTENTIAL ONLY IF THEY ARE CLEARLY SHOWN TO BE ESSENTIAL IN THE MANAGEMENT OF THEIR MEDICAL CONDITION.

Antiepileptic drugs should not be discontinued abruptly in patients in whom the drug is administered to prevent major seizures because of the strong possibility of precipitating status epilepticus with attendant hypoxia and threat to life. In individual cases where the severity and frequency of the seizure disorder are such that the removal of medication does not pose a serious threat to the patient, discontinuation of the drug may be considered prior to and during pregnancy, although it cannot be said with any confidence that even minor seizures do not pose some hazard to the developing embryo or fetus.

Human Data

Congenital Malformations

The North American Antiepileptic Drug Pregnancy Registry reported 16 cases of congenital malformations among the offspring of 149 women with epilepsy who were exposed to valproic acid monotherapy during the first trimester of pregnancy at doses of approximately 1,000 mg per day, for a prevalence rate of 10.7% (95% CI 6.3%-16.9%). Three of the 149 offspring (2%) had neural tube defects and 6 of the 149 (4%) had less severe malformations. Among epileptic women who were exposed to other antiepileptic drug monotherapies during pregnancy (1,048 patients) the malformation rate was 2.9% (95% CI 2.0% to 4.1%). There was a 4-fold increase in congenital malformations among infants with valproic acid-exposed mothers compared with those treated with other antiepileptic monotherapies as a group (Odds Ratio 4.0; 95% CI 2.1 to 7.4). This increased risk does not reflect a comparison versus any specific antiepileptic drug, but the risk versus the heterogeneous group of all other antiepileptic drug monotherapies combined. The increased teratogenic risk from valproic acid in women with epilepsy is expected to be reflected in an increased risk in other indications (e.g., migraine or bipolar disorder).

THE STRONGEST ASSOCIATION OF MATERNAL VALPROATE USAGE WITH CONGENITAL MALFORMATIONS IS WITH NEURAL TUBE DEFECTS (AS DISCUSSED UNDER THE NEXT SUBHEADING). HOWEVER, OTHER CONGENITAL ANOMALIES (E.G. CRANIOFACIAL DEFECTS, CARDIOVASCULAR MALFORMATIONS AND ANOMALIES INVOLVING VARIOUS BODY SYSTEMS), COMPATIBLE AND INCOMPATIBLE WITH LIFE, HAVE BEEN REPORTED. SUFFICIENT DATA TO DETERMINE THE INCIDENCE OF THESE CONGENITAL ANOMALIES IS NOT AVAILABLE.

Neural Tube Defects

THE INCIDENCE OF NEURAL TUBE DEFECTS IN THE FETUS IS INCREASED IN MOTHERS RECEIVING VALPROATE DURING THE FIRST TRIMESTER OF PREGNANCY. THE CENTERS FOR DISEASE CONTROL (CDC) HAS ESTIMATED THE RISK OF VALPROIC ACID EXPOSED WOMEN HAVING CHILDREN WITH SPINA BIFIDA TO BE APPROXIMATELY 1 TO 2%. THE AMERICAN COLLEGE OF OBSTETRICIANS AND GYNECOLOGISTS (ACOG) ESTIMATES THE GENERAL POPULATION RISK FOR CONGENITAL NEURAL TUBE DEFECTS AS 0.14% TO 0.2%.

Tests to detect neural tube and other defects using current accepted procedures should be considered a part of routine prenatal care in pregnant women receiving valproate.

Evidence suggests that pregnant women who receive folic acid supplementation may be at decreased risk for congenital neural tube defects in their offspring compared to pregnant women not receiving folic acid. Whether the risk of neural tube defects in the offspring of women receiving valproate specifically is reduced by folic acid supplementation is unknown. DIETARY FOLIC ACID SUPPLEMENTATION BOTH PRIOR TO AND DURING PREGNANCY SHOULD BE ROUTINELY RECOMMENDED TO PATIENTS CONTEMPLATING PREGNANCY.

Other Adverse Pregnancy Effects

PATIENTS TAKING VALPROATE MAY DEVELOP CLOTTING ABNORMALITIES (SEE and). A PATIENT WHO HAD LOW FIBRINOGEN WHEN TAKING MULTIPLE ANTICONVULSANTS INCLUDING VALPROATE GAVE BIRTH TO AN INFANT WITH AFIBRINOGENEMIA WHO SUBSEQUENTLY DIED OF HEMORRHAGE. IF VALPROATE IS USED IN PREGNANCY, THE CLOTTING PARAMETERS SHOULD BE MONITORED CAREFULLY. PRECAUTIONS - GENERALWARNINGS

PATIENTS TAKING VALPROATE MAY DEVELOP HEPATIC FAILURE (SEE and). FATAL HEPATIC FAILURES, IN A NEWBORN AND IN AN INFANT, HAVE BEEN REPORTED FOLLOWING THE MATERNAL USE OF VALPROATE DURING PREGNANCY. PRECAUTIONS - HEPATOTOXICITYBOXED WARNING

There have been reports of developmental delay, autism and/or autism spectrum disorder in the offspring of women exposed to valproate during pregnancy.

Animal Data

Animal studies have demonstrated valproate-induced teratogenicity. Increased frequencies of malformations, as well as intrauterine growth retardation and death, have been observed in mice, rats, rabbits, and monkeys following prenatal exposure to valproate. Malformations of the skeletal system are the most common structural abnormalities produced in experimental animals, but neural tube closure defects have been seen in mice exposed to maternal plasma valproate concentrations exceeding 230 μg/mL (2.3 times the upper limit of the human therapeutic range) during susceptible periods of embryonic development. Administration of an oral dose of 200 mg/kg/day or greater (50% of the maximum human daily dose or greater on a mg/m basis) to pregnant rats during organogenesis produced malformations (skeletal, cardiac, and urogenital) and growth retardation in the offspring. These doses resulted in peak maternal plasma valproate levels of approximately 340 μg/mL or greater (3.4 times the upper limit of the human therapeutic range or greater). Behavioral deficits have been reported in the offspring of rats given a dose of 200 mg/kg/day throughout most of pregnancy. An oral dose of 350 mg/kg/day (approximately 2 times the maximum human daily dose on a mg/m basis) produced skeletal and visceral malformations in rabbits exposed during organogenesis. Skeletal malformations, growth retardation, and death were observed in rhesus monkeys following administration of an oral dose of 200 mg/kg/day (equal to the maximum human daily dose on a mg/m basis) during organogenesis. This dose resulted in peak maternal plasma valproate levels of approximately 280 μg/mL (2.8 times the upper limit of the human therapeutic range).^2^2^2

Pancreatitis

Cases of life-threatening pancreatitis have been reported in both children and adults receiving valproate. Some of the cases have been described as hemorrhagic with rapid progression from initial symptoms to death. Some cases have occurred shortly after initial use as well as after several years of use. The rate based upon the reported cases exceeds that expected in the general population and there have been cases in which pancreatitis recurred after rechallenge with valproate. In clinical trials, there were 2 cases of pancreatitis without alternative etiology in 2416 patients, representing 1044 patient-years experience. Patients and guardians should be warned that abdominal pain, nausea, vomiting, and/or anorexia can be symptoms of pancreatitis that require prompt medical evaluation. If pancreatitis is diagnosed, valproate should ordinarily be discontinued. Alternative treatment for the underlying medical condition should be initiated as clinically indicated (see). BOXED WARNING

Urea Cycle Disorders (UCD)

Valproic acid is contraindicated in patients with known urea cycle disorders.

Hyperammonemic encephalopathy, sometimes fatal, has been reported following initiation of valproate therapy in patients with urea cycle disorders, a group of uncommon genetic abnormalities, particularly ornithine transcarbamylase deficiency. Prior to the initiation of valproate therapy, evaluation for UCD should be considered in the following patients: 1) those with a history of unexplained encephalopathy or coma, encephalopathy associated with a protein load, pregnancy-related or postpartum encephalopathy, unexplained mental retardation, or history of elevated plasma ammonia or glutamine; 2) those with cyclical vomiting and lethargy, episodic extreme irritability, ataxia, low BUN, or protein avoidance; 3) those with a family history of UCD or a family history of unexplained infant deaths (particularly males); 4) those with other signs or symptoms of UCD. Patients who develop symptoms of unexplained hyperammonemic encephalopathy while receiving valproate therapy should receive prompt treatment (including discontinuation of valproate therapy) and be evaluated for underlying urea cycle disorders (see and). CONTRAINDICATIONSPRECAUTIONS

Suicidal Behavior and Ideation

Antiepileptic drugs (AEDs), including valproic acid, increase the risk of suicidal thoughts or behavior in patients taking these drugs for any indication. Patients treated with any AED for any indication should be monitored for the emergence or worsening of depression, suicidal thoughts or behavior, and/or any unusual changes in mood or behavior.

Pooled analyses of 199 placebo-controlled clinical trials (mono- and adjunctive therapy) of 11 different AEDs showed that patients randomized to one of the AEDs had approximately twice the risk (adjusted Relative Risk 1.8, 95% CI:1.2, 2.7) of suicidal thinking or behavior compared to patients randomized to placebo. In these trials, which had a median treatment duration of 12 weeks, the estimated incidence rate of suicidal behavior or ideation among 27,863 AED-treated patients was 0.43%, compared to 0.24% among 16,029 placebo-treated patients, representing an increase of approximately one case of suicidal thinking or behavior for every 530 patients treated. There were four suicides in drug-treated patients in the trials and none in placebo-treated patients, but the number is too small to allow any conclusion about drug effect on suicide.

The increased risk of suicidal thoughts or behavior with AEDs was observed as early as one week after starting drug treatment with AEDs and persisted for the duration of treatment assessed. Because most trials included in the analysis did not extend beyond 24 weeks, the risk of suicidal thoughts or behavior beyond 24 weeks could not be assessed.

The risk of suicidal thoughts or behavior was generally consistent among drugs in the data analyzed. The finding of increased risk with AEDs of varying mechanisms of action and across a range of indications suggests that the risk applies to all AEDs used for any indication. The risk did not vary substantially by age (5-100 years) in the clinical trials analyzed. Table 1 shows absolute and relative risk by indication for all evaluated AEDs.

Table 1

Risk by indication for antiepileptic drugs in the pooled analysis

Indication | Placebo Patients with Events Per 1000 Patients | Drug Patients with Events Per 1000 Patients | Incidence of Events in Drug Patients/Incidence in Placebo Patients; Relative Risk: | Additional Drug Patients with Events Per 1000 Patients; Risk Difference:
Epilepsy | 1.0 | 3.4 | 3.5 | 2.4
Psychiatric | 5.7 | 8.5 | 1.5 | 2.9
Other | 1.0 | 1.8 | 1.9 | 0.9
Total | 2.4 | 4.3 | 1.8 | 1.9

The relative risk for suicidal thoughts or behavior was higher in clinical trials for epilepsy than in clinical trials for psychiatric or other conditions, but the absolute risk differences were similar for the epilepsy and psychiatric indications.

Anyone considering prescribing valproic acid or any other AED must balance the risk of suicidal thoughts or behavior with the risk of untreated illness. Epilepsy and many other illnesses for which AEDs are prescribed are themselves associated with morbidity and mortality and an increased risk of suicidal thoughts and behavior. Should suicidal thoughts and behavior emerge during treatment, the prescriber needs to consider whether the emergence of these symptoms in any given patient may be related to the illness being treated.

Patients, their caregivers, and families should be informed that AEDs increase the risk of suicidal thoughts and behavior and should be advised of the need to be alert for the emergence or worsening of the signs and symptoms of depression, any unusual changes in mood or behavior, or the emergence of suicidal thoughts, behavior, or thoughts about self-harm. Behaviors of concern should be reported immediately to healthcare providers.

Interaction with Carbapenem Antibiotics

Carbapenem antibiotics (ertapenem, imipenem, meropenem) may reduce serum valproic acid concentrations to subtherapeutic levels, resulting in loss of seizure control. Serum valproic acid concentrations should be monitored frequently after initiating carbapenem therapy. Alternative antibacterial or anticonvulsant therapy should be considered if serum valproic acid concentrations drop significantly or seizure control deteriorates (see). PRECAUTIONS - Drug Interactions

Somnolence in the Elderly

In a double-blind, multicenter trial of valproate in elderly patients with dementia (mean age = 83 years), doses were increased by 125 mg/day to a target dose of 20 mg/kg/day. A significantly higher proportion of valproate patients had somnolence compared to placebo, and although not statistically significant, there was a higher proportion of patients with dehydration. Discontinuations for somnolence were also significantly higher than with placebo. In some patients with somnolence (approximately one-half), there was associated reduced nutritional intake and weight loss. There was a trend for the patients who experienced these events to have a lower baseline albumin concentration, lower valproate clearance, and a higher BUN. In elderly patients, dosage should be increased more slowly and with regular monitoring for fluid and nutritional intake, dehydration, somnolence, and other adverse events. Dose reductions or discontinuation of valproate should be considered in patients with decreased food or fluid intake and in patients with excessive somnolence (see). DOSAGE AND ADMINISTRATION

Thrombocytopenia

The frequency of adverse effects (particularly elevated liver enzymes and thrombocytopenia (see) may be dose-related. In a clinical trial of divalproex sodium as monotherapy in patients with epilepsy, 34/126 patients (27%) receiving approximately 50 mg/kg/day on average, had at least one value of platelets ≤ 75 x 109/L. Approximately half of these patients had treatment discontinued, with return of platelet counts to normal. In the remaining patients, platelet counts normalized with continued treatment. In this study, the probability of thrombocytopenia appeared to increase significantly at total valproate concentrations of ≥ 110 μg/mL (females) or ≥ 135 μg/mL (males). The therapeutic benefit which may accompany the higher doses should therefore be weighed against the possibility of a greater incidence of adverse effects. PRECAUTIONS

PRECAUTIONS

Hepatic Dysfunction

See , , and . BOXED WARNINGCONTRAINDICATIONSWARNINGS

Pancreatitis

See and . BOXED WARNINGWARNINGS

Hypothermia

Hypothermia, defined as an unintentional drop in body core temperature to <35°C (95°F), has been reported in association with valproate therapy both in conjunction with and in the absence of hyperammonemia. This adverse reaction can also occur in patients using concomitant topiramate with valproate after starting topiramate treatment or after increasing the daily dose of topiramate (see). Consideration should be given to stopping valproate in patients who develop hypothermia, which may be manifested by a variety of clinical abnormalities including lethargy, confusion, coma, and significant alterations in other major organ systems such as the cardiovascular and respiratory systems. Clinical management and assessment should include examination of blood ammonia levels. Drug Interactions - Topiramate

Hyperammonemia

Hyperammonemia has been reported in association with valproate therapy and may be present despite normal liver function tests. In patients who develop unexplained lethargy and vomiting or changes in mental status, hyperammonemic encephalopathy should be considered and an ammonia level should be measured. Hyperammonemia should also be considered in patients who present with hypothermia (see). If ammonia is increased, valproate therapy should be discontinued. Appropriate interventions for treatment of hyperammonemia should be initiated, and such patients should undergo investigation for underlying urea cycle disorders (see and and). PRECAUTIONS - Hypothermia CONTRAINDICATIONSWARNINGS - Urea Cycle Disorders (UCD) PRECAUTIONS - Hyperammonemia and Encephalopathy Associated with Concomitant Topiramate Use

Asymptomatic elevations of ammonia are more common and when present, require close monitoring of plasma ammonia levels. If the elevation persists, discontinuation of valproate therapy should be considered.

Hyperammonemia and Encephalopathy Associated with Concomitant Topiramate Use

Concomitant administration of topiramate and valproic acid has been associated with hyperammonemia with or without encephalopathy in patients who have tolerated either drug alone. Clinical symptoms of hyperammonemic encephalopathy often include acute alterations in level of consciousness and/or cognitive function with lethargy or vomiting. Hypothermia can also be a manifestation of hyperammonemia (see). In most cases, symptoms and signs abated with discontinuation of either drug. This adverse event is not due to a pharmacokinetic interaction. It is not known if topiramate monotherapy is associated with hyperammonemia. Patients with inborn errors of metabolism or reduced hepatic mitochondrial activity may be at an increased risk for hyperammonemia with or without encephalopathy. Although not studied, an interaction of topiramate and valproic acid may exacerbate existing defects or unmask deficiencies in susceptible persons. In patients who develop unexplained lethargy, vomiting, or changes in mental status, hyperammonemic encephalopathy should be considered and an ammonia level should be measured. (see and and). PRECAUTIONS - Hypothermia CONTRAINDICATIONSWARNINGS - Urea Cycle Disorders PRECAUTIONS - Hyperammonemia

General

Because of reports of thrombocytopenia (see), inhibition of the secondary phase of platelet aggregation, and abnormal coagulation parameters, (e.g., low fibrinogen), platelet counts and coagulation tests are recommended before initiating therapy and at periodic intervals. It is recommended that patients receiving valproic acid be monitored for platelet count and coagulation parameters prior to planned surgery. In a clinical trial of divalproex sodium as monotherapy in patients with epilepsy, 34/126 patients (27%) receiving approximately 50 mg/kg/day on average, had at least one value of platelets ≤ 75 x 109/L. Approximately half of these patients had treatment discontinued, with return of platelet counts to normal. In the remaining patients, platelet counts normalized with continued treatment. In this study, the probability of thrombocytopenia appeared to increase significantly at total valproate concentrations of ≤ 110 µg/mL (females) or ≥ 135 µg/mL (males). Evidence of hemorrhage, bruising, or a disorder of hemostasis/coagulation is an indication for reduction of the dosage or withdrawal of therapy. WARNINGS

Since valproate may interact with concurrently administered drugs which are capable of enzyme induction, periodic plasma concentration determinations of valproate and concomitant drugs are recommended during the early course of therapy (see). PRECAUTIONS - Drug Interactions

Valproate is partially eliminated in the urine as a keto-metabolite which may lead to a false interpretation of the urine ketone test.

There have been reports of altered thyroid function tests associated with valproate. The clinical significance of these is unknown.

There are studies that suggest valproate stimulates the replication of the HIV and CMV viruses under certain experimental conditions. The clinical consequence, if any, is not known. Additionally, the relevance of these findings is uncertain for patients receiving maximally suppressive antiretroviral therapy. Nevertheless, these data should be borne in mind when interpreting the results from regular monitoring of the viral load in HIV infected patients receiving valproate or when following CMV infected patients clinically. in vitroin vitro

Multi-organ Hypersensitivity Reaction

Multi-organ hypersensitivity reactions have been rarely reported in close temporal association to the initiation of valproate therapy in adult and pediatric patients (median time to detection 21 days: range 1 to 40 days). Although there have been a limited number of reports, many of these cases resulted in hospitalization and at least one death has been reported. Signs and symptoms of this disorder were diverse; however, patients typically, although not exclusively, presented with fever and rash associated with other organ system involvement. Other associated manifestations may include lymphadenopathy, hepatitis, liver function test abnormalities, hematological abnormalities (e.g., eosinophilia, thrombocytopenia, neutropenia), pruritis, nephritis, oliguria, hepato-renal syndrome, arthralgia, and asthenia. Because the disorder is variable in its expression, other organ system symptoms and signs, not noted here, may occur. If this reaction is suspected, valproate should be discontinued and an alternative treatment started. Although the existence of cross sensitivity with other drugs that produce this syndrome is unclear, the experience amongst drugs associated with multi-organ hypersensitivity would indicate this to be a possibility.

Information for patients

Since valproic acid has been associated with certain types of birth defects, female patients of childbearing age considering the use of valproic acid should be advised of the risk and of alternative therapeutic options and to read the , which appears as the last section of the labeling. Patient Information Leaflet This is especially important when the treatment of a spontaneously reversible condition not ordinarily associated with permanent injury or risk of death (e.g., migraine) is considered.

Patients should be encouraged to enroll in the North American Antiepileptic Drug (NAAED) Pregnancy Registry if they become pregnant. This registry is collecting information about the safety of antiepileptic drugs during pregnancy. To enroll, patients can call the toll free number 1-888-233-2334 (see). PRECAUTIONS - Pregnancy

Patients and guardians should be warned that abdominal pain, nausea, vomiting, and/or anorexia can be symptoms of pancreatitis and, therefore, require further medical evaluation promptly.

Suicidal Thinking and Behavior

Patients, their caregivers, and families should be counseled that AEDs, including valproic acid, may increase the risk of suicidal thoughts and behavior and should be advised of the need to be alert for the emergence or worsening of symptoms of depression, any unusual changes in mood or behavior, or the emergence of suicidal thoughts, behavior, or thoughts about self-harm. Behaviors of concern should be reported immediately to the healthcare providers (see). WARNINGS

Patients should be informed of the signs and symptoms associated with hyperammonemic encephalopathy (see) and be told to inform the prescriber if any of these symptoms occur. PRECAUTIONS - Hyperammonemia

Since valproic acid products may produce CNS depression, especially when combined with another CNS depressant (e.g., alcohol), patients should be advised not to engage in hazardous activities, such as driving an automobile or operating dangerous machinery, until it is known that they do not become drowsy from the drug.

Patients should be instructed that a fever associated with other organ system involvement (rash, lymphadenopathy, etc.) may be drug-related and should be reported to the physician immediately (see). PRECAUTIONS - Multi-organ Hypersensitivity Reaction

Drug Interactions

Effects of Co-Administered Drugs on Valproate Clearance

Drugs that affect the level of expression of hepatic enzymes, particularly those that elevate levels of glucuronosyltransferases, may increase the clearance of valproate. For example, phenytoin, carbamazepine, and phenobarbital (or primidone) can double the clearance of valproate. Thus, patients on monotherapy will generally have longer half-lives and higher concentrations than patients receiving polytherapy with antiepilepsy drugs.

In contrast, drugs that are inhibitors of cytochrome P450 isozymes, e.g., antidepressants, may be expected to have little effect on valproate clearance because cytochrome P450 microsomal mediated oxidation is a relatively minor secondary metabolic pathway compared to glucuronidation and beta-oxidation.

Because of these changes in valproate clearance, monitoring of valproate and concomitant drug concentrations should be increased whenever enzyme inducing drugs are introduced or withdrawn.

The following list provides information about the potential for an influence of several commonly prescribed medications on valproate pharmacokinetics. The list is not exhaustive nor could it be, since new interactions are continuously being reported.

Drugs for Which a Potentially Important Interaction Has Been Observed

Aspirin

A study involving the co-administration of aspirin at antipyretic doses (11 to 16 mg/kg) with valproate to pediatric patients (n = 6) revealed a decrease in protein binding and an inhibition of metabolism of valproate. Valproate free fraction was increased 4-fold in the presence of aspirin compared to valproate alone. The ß-oxidation pathway consisting of 2-E-valproic acid, 3-OH-valproic acid, and 3-keto valproic acid was decreased from 25% of total metabolites excreted on valproate alone to 8.3% in the presence of aspirin. Caution should be observed if valproate and aspirin are to be co-administered.

Felbamate

A study involving the co-administration of 1200 mg/day of felbamate with valproate to patients with epilepsy (n = 10) revealed an increase in mean valproate peak concentration by 35% (from 86 to 115 μg/mL) compared to valproate alone. Increasing the felbamate dose to 2400 mg/day increased the mean valproate peak concentration to 133 μg/mL (another 16% increase). A decrease in valproate dosage may be necessary when felbamate therapy is initiated.

Carbapenem Antibiotics

A clinically significant reduction in serum valproic acid concentration has been reported in patients receiving carbapenem antibiotics (ertapenem, imipenem, meropenem) and may result in loss of seizure control. The mechanism of this interaction is not well understood. Serum valproic acid concentrations should be monitored frequently after initiating carbapenem therapy. Alternative antibacterial or anticonvulsant therapy should be considered if serum valproic acid concentrations drop significantly or seizure control deteriorates (See). WARNINGS

Rifampin

A study involving the administration of a single dose of valproate (7 mg/kg) 36 hours after 5 nights of daily dosing with rifampin (600 mg) revealed a 40% increase in the oral clearance of valproate. Valproate dosage adjustment may be necessary when it is co-administered with rifampin.

Drugs for Which Either No Interaction or a Likely Clinically Unimportant Interaction Has Been Observed

Antacids

A study involving the co-administration of valproate 500 mg with commonly administered antacids (Maalox, Trisogel, and Titralac - 160 mEq doses) did not reveal any effect on the extent of absorption of valproate.

Chlorpromazine

A study involving the administration of 100 to 300 mg/day of chlorpromazine to schizophrenic patients already receiving valproate (200 mg BID) revealed a 15% increase in trough plasma levels of valproate.

Haloperidol

A study involving the administration of 6 to 10 mg/day of haloperidol to schizophrenic patients already receiving valproate (200 mg BID) revealed no significant changes in valproate trough plasma levels.

Cimetidine and ranitidine do not affect the clearance of valproate.

Effects of Valproate on Other Drugs

Valproate has been found to be a weak inhibitor of some P450 isozymes, epoxide hydrase, and glucuronyltransferases.

The following list provides information about the potential for an influence of valproate coadministration on the pharmacokinetics or pharmacodynamics of several commonly prescribed medications. The list is not exhaustive, since new interactions are continuously being reported.

Drugs for Which a Potentially Important Valproate Interaction Has Been Observed

Amitriptyline/Nortriptyline

Administration of a single oral 50 mg dose of amitriptyline to 15 normal volunteers (10 males and 5 females) who received valproate (500 mg BID) resulted in a 21% decrease in plasma clearance of amitriptyline and a 34% decrease in the net clearance of nortriptyline. Rare postmarketing reports of concurrent use of valproate and amitriptyline resulting in an increased amitriptyline level have been received. Concurrent use of valproate and amitriptyline has rarely been associated with toxicity. Monitoring of amitriptyline levels should be considered for patients taking valproate concomitantly with amitriptyline. Consideration should be given to lowering the dose of amitriptyline/nortriptyline in the presence of valproate.

Carbamazepine/carbamazepine-10,11-Epoxide

Serum levels of carbamazepine (CBZ) decreased 17% while that of carbamazepine-10,11-epoxide (CBZ-E) increased by 45% upon coadministration of valproate and CBZ to epileptic patients.

Clonazepam

The concomitant use of valproic acid and clonazepam may induce absence status in patients with a history of absence type seizures.

Diazepam

Valproate displaces diazepam from its plasma albumin binding sites and inhibits its metabolism. Co-administration of valproate (1500 mg daily) increased the free fraction of diazepam (10 mg) by 90% in healthy volunteers (n = 6). Plasma clearance and volume of distribution for free diazepam were reduced by 25% and 20%, respectively, in the presence of valproate. The elimination half-life of diazepam remained unchanged upon addition of valproate.

Ethosuximide

Valproate inhibits the metabolism of ethosuximide. Administration of a single ethosuximide dose of 500 mg with valproate (800 to 1600 mg/day) to healthy volunteers (n = 6) was accompanied by a 25% increase in elimination half-life of ethosuximide and a 15% decrease in its total clearance as compared to ethosuximide alone. Patients receiving valproate and ethosuximide, especially along with other anticonvulsants, should be monitored for alterations in serum concentrations of both drugs.

Lamotrigine

In a steady-state study involving 10 healthy volunteers, the elimination half-life of lamotrigine increased from 26 to 70 hours with valproate co-administration (a 165% increase). The dose of lamotrigine should be reduced when co-administered with valproate. Serious skin reactions (such as Stevens-Johnson Syndrome and toxic epidermal necrolysis) have been reported with concomitant lamotrigine and valproate administration. See lamotrigine package insert for details on lamotrigine dosing with concomitant valproate administration.

Phenobarbital

Valproate was found to inhibit the metabolism of phenobarbital. Co-administration of valproate (250 mg BID for 14 days) with phenobarbital to normal subjects (n = 6) resulted in a 50% increase in half-life and a 30% decrease in plasma clearance of phenobarbital (60 mg single-dose). The fraction of phenobarbital dose excreted unchanged increased by 50% in presence of valproate.

There is evidence for severe CNS depression, with or without significant elevations of barbiturate or valproate serum concentrations. All patients receiving concomitant barbiturate therapy should be closely monitored for neurological toxicity. Serum barbiturate concentrations should be obtained, if possible, and the barbiturate dosage decreased, if appropriate.

Primidone, which is metabolized to a barbiturate, may be involved in a similar interaction with valproate.

Phenytoin

Valproate displaces phenytoin from its plasma albumin binding sites and inhibits its hepatic metabolism. Co-administration of valproate (400 mg TID) with phenytoin (250 mg) in normal volunteers (n = 7) was associated with a 60% increase in the free fraction of phenytoin. Total plasma clearance and apparent volume of distribution of phenytoin increased 30% in the presence of valproate. Both the clearance and apparent volume of distribution of free phenytoin were reduced by 25%.

In patients with epilepsy, there have been reports of breakthrough seizures occurring with the combination of valproate and phenytoin. The dosage of phenytoin should be adjusted as required by the clinical situation.

Tolbutamide

From in vitro experiments, the unbound fraction of tolbutamide was increased from 20% to 50% when added to plasma samples taken from patients treated with valproate. The clinical relevance of this displacement is unknown.

Topiramate

Concomitant administration of valproic acid and topiramate has been associated with hyperammonemia with and without encephalopathy (see and and and). Concomitant administration of topiramate with valproic acid has also been associated with hypothermia in patients who have tolerated either drug alone. It may be prudent to examine blood ammonia levels in patients in whom the onset of hypothermia has been reported (see and). CONTRAINDICATIONSWARNINGS - Urea Cycle Disorders PRECAUTIONS - Hyperammonemia- Hyperammonemia and Encephalopathy Associated with Concomitant Topiramate Use PRECAUTIONS - Hypothermia Hyperammonemia

Warfarin

In an study, valproate increased the unbound fraction of warfarin by up to 32.6%. The therapeutic relevance of this is unknown; however, coagulation tests should be monitored if valproic acid therapy is instituted in patients taking anticoagulants. in vitro

Zidovudine

In six patients who were seropositive for HIV, the clearance of zidovudine (100 mg q8h) was decreased by 38% after administration of valproate (250 or 500 mg q8h); the half-life of zidovudine was unaffected.

Drugs for Which Either No Interaction or a Likely Clinically Unimportant Interaction Has Been Observed

Acetaminophen

Valproate had no effect on any of the pharmacokinetic parameters of acetaminophen when it was concurrently administered to three epileptic patients.

Clozapine

In psychotic patients (n = 11), no interaction was observed when valproate was coadministered with clozapine.

Lithium

Co-administration of valproate (500 mg BID) and lithium carbonate (300 mg TID) to normal male volunteers (n = 16) had no effect on the steady-state kinetics of lithium.

Lorazepam

Concomitant administration of valproate (500 mg BID) and lorazepam (1 mg BID) in normal male volunteers (n = 9) was accompanied by a 17% decrease in the plasma clearance of lorazepam.

Oral Contraceptive Steroids

Administration of a single-dose of ethinyloestradiol (50 μg)/levonorgestrel (250 μg) to 6 women on valproate (200 mg BID) therapy for 2 months did not reveal any pharmacokinetic interaction.

Carcinogenesis, mutagenesis, impairment of fertility

Carcinogenesis

Valproic acid was administered orally to Sprague Dawley rats and ICR (HA/ICR) mice at doses of 80 and 170 mg/kg/day (approximately 10 to 50% of the maximum human daily dose on a mg/m basis) for two years. A variety of neoplasms were observed in both species. The chief findings were a statistically significant increase in the incidence of subcutaneous fibrosarcomas in high dose male rats receiving valproic acid and a statistically significant dose-related trend for benign pulmonary adenomas in male mice receiving valproic acid. The significance of these findings for humans is unknown.^2

Mutagenesis

Valproate was not mutagenic in an in vitro bacterial assay (Ames test), did not produce dominant lethal effects in mice, and did not increase chromosome aberration frequency in an in vivo cytogenetic study in rats. Increased frequencies of sister chromatid exchange (SCE) have been reported in a study of epileptic children taking valproate, but this association was not observed in another study conducted in adults. There is some evidence that increased SCE frequencies may be associated with epilepsy. The biological significance of an increase in SCE frequency is not known.

Fertility

Chronic toxicity studies in juvenile and adult rats and dogs demonstrated reduced spermatogenesis and testicular atrophy at oral doses of 400 mg/kg/day or greater in rats (approximately equivalent to or greater than the maximum human daily dose on a mg/m basis) and 150 mg/kg/day or greater in dogs (approximately 1.4 times the maximum human daily dose or greater on a mg/m basis). Segment I fertility studies in rats have shown oral doses up to 350 mg/kg/day (approximately equal to the maximum human daily dose on a mg/m basis) for 60 days to have no effect on fertility. THE EFFECT OF VALPROATE ON TESTICULAR DEVELOPMENT AND ON SPERM PRODUCTION AND FERTILITY IN HUMANS IS UNKNOWN.^2^2^2

Pregnancy

Pregnancy Category D: See . WARNINGS

To provide information regarding the effects of exposure to valproic acid, healthcare providers are advised to recommend that pregnant patients taking valproic acid enroll in the NAAED Pregnancy Registry. This can be done by calling the toll free number 1-888-233-2334, and must be done by patients themselves. Information on the registry can also be found at the website http://www.aedpregnancyregistry.org/. in utero

Nursing mothers

Valproate is excreted in breast milk. Concentrations in breast milk have been reported to be 1-10% of serum concentrations. It is not known what effect this would have on a nursing infant. Consideration should be given to discontinuing nursing when valproic acid is administered to a nursing woman.

Pediatric use

Experience has indicated that pediatric patients under the age of two years are at a considerably increased risk of developing fatal hepatotoxicity, especially those with the aforementioned conditions (see). When valproic acid is used in this patient group, it should be used with extreme caution and as a sole agent. The benefits of therapy should be weighed against the risks. Above the age of 2 years, experience in epilepsy has indicated that the incidence of fatal hepatotoxicity decreases considerably in progressively older patient groups. BOXED WARNING

Younger children, especially those receiving enzyme-inducing drugs, will require larger maintenance doses to attain targeted total and unbound valproic acid concentrations.

The variability in free fraction limits the clinical usefulness of monitoring total serum valproic acid concentrations. Interpretation of valproic acid concentrations in children should include consideration of factors that affect hepatic metabolism and protein binding.

The basic toxicology and pathologic manifestations of valproate sodium in neonatal (4-day old) and juvenile (14-day old) rats are similar to those seen in young adult rats. However, additional findings, including renal alterations in juvenile rats and renal alterations and retinal dysplasia in neonatal rats, have been reported. These findings occurred at 240 mg/kg/day, a dosage approximately equivalent to the human maximum recommended daily dose on a mg/m basis. They were not seen at 90 mg/kg, or 40% of the maximum human daily dose on a mg/m basis.^2^2

Geriatric use

No patients above the age of 65 years were enrolled in double-blind prospective clinical trials of mania associated with bipolar illness. In a case review study of 583 patients, 72 patients (12%) were greater than 65 years of age. A higher percentage of patients above 65 years of age reported accidental injury, infection, pain, somnolence, and tremor. Discontinuation of valproate was occasionally associated with the latter two events. It is not clear whether these events indicate additional risk or whether they result from preexisting medical illness and concomitant medication use among these patients.

A study of elderly patients with dementia revealed drug related somnolence and discontinuation for somnolence (see). The starting dose should be reduced in these patients, and dosage reductions or discontinuation should be considered in patients with excessive somnolence (see). WARNINGS - Somnolence in the Elderly DOSAGE AND ADMINISTRATION

ADVERSE REACTIONS

To report SUSPECTED ADVERSE REACTIONS, contact Hi-Tech Pharmacal Co., Inc. at 1-800-262-9010 or FDA at 1-800-FDA-1088 or www.fda.gov/medwatch.

Epilepsy

The data described in the following section were obtained using divalproex sodium tablets.

Based on a placebo-controlled trial of adjunctive therapy for treatment of complex partial seizures, divalproex sodium was generally well tolerated with most adverse events rated as mild to moderate in severity. Intolerance was the primary reason for discontinuation in the divalproex sodium-treated patients (6%), compared to 1% of placebo-treated patients.

Table 2 lists treatment-emergent adverse events which were reported by ≥ 5% of divalproex sodium-treated patients and for which the incidence was greater than in the placebo group, in a placebo-controlled trial of adjunctive therapy for the treatment of complex partial seizures. Since patients were also treated with other antiepilepsy drugs, it is not possible, in most cases, to determine whether the following adverse events can be ascribed to divalproex sodium alone, or the combination of divalproex sodium and other antiepilepsy drugs.

Table 2
≥ Adverse Events Reported by 5% of Patients Treated
with Divalproex Sodium During Placebo-Controlled Trial of
Adjunctive Therapy for Complex Partial Seizures
Body System/Even | Divalproex Sodium (%); (n = 77) | Placebo (%); (n = 70)
Body as a Whole
Headache | 31 | 21
Asthenia | 27 | 7
Fever | 6 | 4
Gastrointestinal System
Nausea | 48 | 14
Vomiting | 27 | 7
Abdominal Pain | 23 | 6
Diarrhea | 13 | 6
Anorexia | 12 | 0
Dyspepsia | 8 | 4
Constipation | 5 | 1
Nervous System
Somnolence | 27 | 11
Tremor | 25 | 6
Dizziness | 25 | 13
Diplopia | 16 | 9
Amblyopia/Blurred Vision | 12 | 9
Ataxia | 8 | 1
Nystagmus | 8 | 1
Emotional Lability | 6 | 4
Thinking Abnormal | 6 | 0
Amnesia | 5 | 1
Respiratory System
Flu Syndrome | 12 | 9
Infection | 12 | 6
Bronchitis | 5 | 1
Rhinitis | 5 | 4
Other
Alopecia | 6 | 1
Weight Loss | 6 | 0

Table 3 lists treatment-emergent adverse events which were reported by ≥ 5% of patients in the high dose divalproex sodium group, and for which the incidence was greater than in the low dose group, in a controlled trial of divalproex sodium monotherapy treatment of complex partial seizures. Since patients were being titrated off another antiepilepsy drug during the first portion of the trial, it is not possible, in many cases, to determine whether the following adverse events can be ascribed to divalproex sodium alone, or the combination of divalproex sodium and other antiepilepsy drugs.

Table 3
≥ Adverse Events Reported by 5% of Patients in the High Dose
Group in the Controlled Trial of Divalproex Sodium Monotherapy for
Complex Partial Seizures^1 [1 Headache was the only adverse event that occurred in ≥ 5% of patients in the high dose group and at an equal or greater incidence in the low dose group.]
Body System/Event | High Dose (%); (n = 131) | Low Dose (%); (n = 134)
Body as a Whole
Asthenia | 21 | 10
Digestive System
Nausea | 34 | 26
Diarrhea | 23 | 19
Vomiting | 23 | 15
Abdominal Pain | 12 | 9
Anorexia | 11 | 4
Dyspepsia | 11 | 10
Hemic/Lymphatic System
Thrombocytopenia | 24 | 1
Ecchymosis | 5 | 4
Metabolic/Nutritional
Weight Gain | 9 | 4
Peripheral Edema | 8 | 3
Nervous System
Tremor | 57 | 19
Somnolence | 30 | 18
Dizziness | 18 | 13
Insomnia | 15 | 9
Nervousness | 11 | 7
Amnesia | 7 | 4
Nystagmus | 7 | 1
Depression | 5 | 4
Respiratory System
Infection | 20 | 13
Pharyngitis | 8 | 2
Dyspnea | 5 | 1
Skin and Appendages
Alopecia | 24 | 13
Special Senses
Amblyopia/Blurred Vision | 8 | 4
Tinnitus | 7 | 1

The following additional adverse events were reported by greater than 1% but less than 5% of the 358 patients treated with divalproex sodium in the controlled trials of complex partial seizures:

Body as a Whole:

Back pain, chest pain, malaise.

Cardiovascular System:

Tachycardia, hypertension, palpitation.

Digestive System:

Increased appetite, flatulence, hematemesis, eructation, pancreatitis, periodontal abscess.

Hemic and Lymphatic System:

Petechia.

Metabolic and Nutritional Disorders:

SGOT increased, SGPT increased.

Musculoskeletal System:

Myalgia, twitching, arthralgia, leg cramps, myasthenia.

Nervous System:

Anxiety, confusion, abnormal gait, paresthesia, hypertonia, incoordination, abnormal dreams, personality disorder.

Respiratory System:

Sinusitis, cough increased, pneumonia, epistaxis.

Skin and Appendages:

Rash, pruritus, dry skin.

Special Senses:

Taste perversion, abnormal vision, deafness, otitis media.

Urogenital System:

Urinary incontinence, vaginitis, dysmenorrhea, amenorrhea, urinary frequency.

Other Patient Populations

Adverse events that have been reported with all dosage forms of valproate from epilepsy trials, spontaneous reports, and other sources are listed below by body system.

Gastrointestinal:

The most commonly reported side effects at the initiation of therapy are nausea, vomiting, and indigestion. These effects are usually transient and rarely require discontinuation of therapy. Diarrhea, abdominal cramps, and constipation have been reported. Both anorexia with some weight loss and increased appetite with weight gain have also been reported. The administration of delayed-release divalproex sodium may result in reduction of gastrointestinal side effects in some patients.

CNS Effects:

Sedative effects have occurred in patients receiving valproate alone but occur most often in patients receiving combination therapy. Sedation usually abates upon reduction of other antiepileptic medication. Tremor (may be dose-related), hallucinations, ataxia, headache, nystagmus, diplopia, asterixis, "spots before eyes", dysarthria, dizziness, confusion, hypesthesia, vertigo, incoordination, and Parkinsonism have been reported with the use of valproate. Rare cases of coma have occurred in patients receiving valproate alone or in conjunction with phenobarbital. In rare instances encephalopathy with or without fever has developed shortly after the introduction of valproate monotherapy without evidence of hepatic dysfunction or inappropriately high plasma valproate levels. Although recovery has been described following drug withdrawal, there have been fatalities in patients with hyperammonemic encephalopathy, particularly in patients with underlying urea cycle disorders (see and). WARNINGS - Urea Cycle Disorders PRECAUTIONS

Several reports have noted reversible cerebral atrophy and dementia in association with valproate therapy.

Dermatologic:

Transient hair loss, skin rash, photosensitivity, generalized pruritus, erythema multiforme, and Stevens-Johnson syndrome. Rare cases of toxic epidermal necrolysis have been reported including a fatal case in a 6 month old infant taking valproate and several other concomitant medications. An additional case of toxic epidermal necrosis resulting in death was reported in a 35 year old patient with AIDS taking several concomitant medications and with a history of multiple cutaneous drug reactions. Serious skin reactions have been reported with concomitant administration of lamotrigine and valproate (see). PRECAUTIONS - Drug Interactions

Psychiatric:

Emotional upset, depression, psychosis, aggression, hyperactivity, hostility, and behavioral deterioration.

Musculoskeletal:

Weakness.

Hematologic:

Thrombocytopenia and inhibition of the secondary phase of platelet aggregation may be reflected in altered bleeding time, petechiae, bruising, hematoma formation, epistaxis, and frank hemorrhage (see and). Relative lymphocytosis, macrocytosis, hypofibrinogenemia, leukopenia, eosinophilia, anemia including macrocytic with or without folate deficiency, bone marrow suppression, pancytopenia, aplastic anemia, agranulocytosis, and acute intermittent porphyria. PRECAUTIONS - General Drug Interactions

Hepatic:

Minor elevations of transaminases (e.g., SGOT and SGPT) and LDH are frequent and appear to be dose-related. Occasionally, laboratory test results include increases in serum bilirubin and abnormal changes in other liver function tests. These results may reflect potentially serious hepatotoxicity (see). WARNINGS

Endocrine:

Irregular menses, secondary amenorrhea, breast enlargement, galactorrhea, and parotid gland swelling. Abnormal thyroid function tests (see). PRECAUTIONS

There have been rare spontaneous reports of polycystic ovary disease. A cause and effect relationship has not been established.

Pancreatic:

Acute pancreatitis, including fatalities (see). WARNINGS

Metabolic:

Hyperammonemia (see), hyponatremia, and inappropriate ADH secretion. PRECAUTIONS

There have been rare reports of Fanconi's syndrome occurring chiefly in children.

Decreased carnitine concentrations have been reported although the clinical relevance is undetermined.

Hyperglycinemia has occurred and was associated with a fatal outcome in a patient with preexistent nonketotic hyperglycemia.

Genitourinary:

Enuresis and urinary tract infection.

Special Senses:

Hearing loss, either reversible or irreversible, has been reported; however, a cause and effect relationship has not been established. Ear pain has also been reported.

Other:

Allergic reaction, anaphylaxis, edema of the extremities, lupus erythematosus, bone pain, cough increased, pneumonia, otitis media, bradycardia, cutaneous vasculitis, fever, and hypothermia.

Mania

Although valproic acid has not been evaluated for safety and efficacy in the treatment of manic episodes associated with bipolar disorder, the following adverse events not listed above were reported by 1% or more of patients from two placebo-controlled clinical trials of divalproex sodium tablets.

Body as a Whole:

Chills, neck pain, neck rigidity.

Cardiovascular System:

Hypotension, postural hypotension, vasodilation.

Digestive System:

Fecal incontinence, gastroenteritis, glossitis.

Musculoskeletal System:

Arthrosis.

Nervous System:

Agitation, catatonic reaction, hypokinesia, reflexes increased, tardive dyskinesia, vertigo.

Skin and Appendages:

Furunculosis, maculopapular rash, seborrhea.

Special Senses:

Conjunctivitis, dry eyes, eye pain.

Urogenital System:

Dysuria.

Migraine

Although valproic acid has not been evaluated for safety and efficacy in the treatment of prophylaxis of migraine headaches, the following adverse events not listed above were reported by 1% or more of patients from two placebo-controlled clinical trials of divalproex sodium tablets.

Body as a Whole:

Face edema.

Digestive System:

Dry mouth, stomatitis.

Urogenital System:

Cystitis, metrorrhagia, and vaginal hemorrhage.

OVERDOSAGE

Overdosage with valproate may result in somnolence, heart block, and deep coma. Fatalities have been reported; however, patients have recovered from valproate levels as high as 2120 μg/mL.

In overdose situations, the fraction of drug not bound to protein is high and hemodialysis or tandem hemodialysis plus hemoperfusion may result in significant removal of drug. The benefit of gastric lavage or emesis will vary with the time since ingestion. General supportive measures should be applied with particular attention to the maintenance of adequate urinary output.

Naloxone has been reported to reverse the CNS depressant effects of valproate overdosage. Because naloxone could theoretically also reverse the antiepileptic effects of valproate, it should be used with caution in patients with epilepsy.

DOSAGE AND ADMINISTRATION

Valproic acid is administered orally. Valproic acid is indicated as monotherapy and adjunctive therapy in complex partial seizures in adults and pediatric patients down to the age of 10 years, and in simple and complex absence seizures. As the valproic acid dosage is titrated upward, concentrations of phenobarbital, carbamazepine, and/or phenytoin may be affected (see). PRECAUTIONS - Drug Interactions

Complex Partial Seizures:

For adults and children 10 years of age or older.

Monotherapy (Initial Therapy):

Valproic acid has not been systematically studied as initial therapy. Patients should initiate therapy at 10 to 15 mg/kg/day. The dosage should be increased by 5 to 10 mg/kg/week to achieve optimal clinical response. Ordinarily, optimal clinical response is achieved at daily doses below 60 mg/kg/day. If satisfactory clinical response has not been achieved, plasma levels should be measured to determine whether or not they are in the usually accepted therapeutic range (50 to 100 μg/mL). No recommendation regarding the safety of valproate for use at doses above 60 mg/kg/day can be made.

The probability of thrombocytopenia increases significantly at total trough valproate plasma concentrations above 110 μg/mL in females and 135 μg/mL in males. The benefit of improved seizure control with higher doses should be weighed against the possibility of a greater incidence of adverse reactions.

Conversion to Monotherapy:

Patients should initiate therapy at 10 to 15 mg/kg/day. The dosage should be increased by 5 to 10 mg/kg/week to achieve optimal clinical response. Ordinarily, optimal clinical response is achieved at daily doses below 60 mg/kg/day. If satisfactory clinical response has not been achieved, plasma levels should be measured to determine whether or not they are in the usually accepted therapeutic range (50 to 100 μg/mL). No recommendation regarding the safety of valproate for use at doses above 60 mg/kg/day can be made. Concomitant antiepilepsy drug (AED) dosage can ordinarily be reduced by approximately 25% every 2 weeks. This reduction may be started at initiation of valproic acid therapy, or delayed by 1 to 2 weeks if there is a concern that seizures are likely to occur with a reduction. The speed and duration of withdrawal of the concomitant AED can be highly variable, and patients should be monitored closely during this period for increased seizure frequency.

Adjunctive Therapy:

Valproic acid may be added to the patient's regimen at a dosage of 10 to 15 mg/kg/day. The dosage may be increased by 5 to 10 mg/kg/week to achieve optimal clinical response. Ordinarily, optimal clinical response is achieved at daily doses below 60 mg/kg/day. If satisfactory clinical response has not been achieved, plasma levels should be measured to determine whether or not they are in the usually accepted therapeutic range (50 to 100 μg/mL). No recommendation regarding the safety of valproate for use at doses above 60 mg/kg/day can be made. If the total daily dose exceeds 250 mg, it should be given in divided doses.

In a study of adjunctive therapy for complex partial seizures in which patients were receiving either carbamazepine or phenytoin in addition to divalproex sodium tablets, no adjustment of carbamazepine or phenytoin dosage was needed (see). However, since valproate may interact with these or other concurrently administered AEDs as well as other drugs (see), periodic plasma concentration determinations of concomitant AEDs are recommended during the early course of therapy (see). CLINICAL STUDIESDrug Interactions PRECAUTIONS - Drug Interactions

Simple and Complex Absence Seizures:

The recommended initial dose is 15 mg/kg/day, increasing at one week intervals by 5 to 10 mg/kg/day until seizures are controlled or side effects preclude further increases. The maximum recommended dosage is 60 mg/kg/day. If the total daily dose exceeds 250 mg, it should be given in divided doses.

A good correlation has not been established between daily dose, serum concentrations, and therapeutic effect. However, therapeutic valproate serum concentrations for most patients with absence seizures is considered to range from 50 to 100 μg/mL. Some patients may be controlled with lower or higher serum concentrations (see). CLINICAL PHARMACOLOGY

As the valproic acid dosage is titrated upward, blood concentrations of phenobarbital and/or phenytoin may be affected (see). PRECAUTIONS

Antiepilepsy drugs should not be abruptly discontinued in patients in whom the drug is administered to prevent major seizures because of the strong possibility of precipitating status epilepticus with attendant hypoxia and threat to life.

The following table is a guide for the initial daily dose of valproic acid (15 mg/kg/day):

(Kg) (Lb); Weight |  | Dose (mg); Total; Daily | of Oral Solution; Number of Teaspoonfuls
(Kg) (Lb); Weight |  | Dose (mg); Total; Daily | Dose 1 | Dose 2 | Dose 3
10 - 24.9 | 22 - 54.9 | 250 | 0 | 0 | 1
25 - 39.9 | 55 - 87.9 | 500 | 1 | 0 | 1
40 - 59.9 | 88 - 131.9 | 750 | 1 | 1 | 1
60 - 74.9 | 132 - 164.9 | 1,000 | 1 | 1 | 2
75 - 89.9 | 165 - 197.9 | 1,250 | 2 | 1 | 2

General Dosing Advice

Dosing in Elderly Patients

Due to a decrease in unbound clearance of valproate and possibly a greater sensitivity to somnolence in the elderly, the starting dose should be reduced in these patients. Dosage should be increased more slowly and with regular monitoring for fluid and nutritional intake, dehydration, somnolence, and other adverse events. Dose reductions or discontinuation of valproate should be considered in patients with decreased food or fluid intake and in patients with excessive somnolence. The ultimate therapeutic dose should be achieved on the basis of both tolerability and clinical response (see). WARNINGS

Dose-Related Adverse Events

The frequency of adverse effects (particularly elevated liver enzymes and thrombocytopenia) may be dose-related. The probability of thrombocytopenia appears to increase significantly at total valproate concentrations of ≥ 110 μg/mL (females) or ≥ 135 μg/mL (males) (see). The benefit of improved therapeutic effect with higher doses should be weighed against the possibility of a greater incidence of adverse reactions. PRECAUTIONS

G.I. Irritation

Patients who experience G.I. irritation may benefit from administration of the drug with food or by slowly building up the dose from an initial low level.

PATIENT INFORMATION LEAFLET

Important Information for Women Who Could Become Pregnant About the Use of Valproic Acid Oral Solution, USP

Please read this leaflet carefully before you take valproic acid oral solution, USP. This leaflet provides a summary of important information about taking valproic acid oral solution, USP to women who could become pregnant. If you have any questions or concerns, or want more information about valproic acid oral solution, USP, contact your doctor or pharmacist.

Information for Women Who Could Become Pregnant

Valproic acid oral solution, USP can be obtained only by prescription from your doctor. The decision to use valproic acid oral solution, USP is one that you and your doctor should make together, taking into account your individual needs and medical condition.

Before using valproic acid oral solution, USP, women who can become pregnant should consider the fact that these medications have been associated with birth defects, in particular, with spina bifida and other defects related to failure of the spinal canal to close normally. Approximately 1 to 2% of children born to women with epilepsy taking divalproex sodium in the first 12 weeks of pregnancy had these defects (based on data from the Centers for Disease Control, a U.S. agency based in Atlanta). The incidence in the general population is 0.1 to 0.2%.

Valproic acid oral solution, USP has also been associated with other birth defects such as defects of the heart, the bones, and other parts of the body. Information suggests that birth defects may be more likely to occur with these medications than some other drugs that treat your medical condition.

Information for Women Who Are Planning to Get Pregnant

- Women taking valproic acid oral solution, USP who are planning to get pregnant should discuss the treatment options with their doctor.

Information for Women Who Become Pregnant

- If you become pregnant while taking valproic acid oral solution, USP you should contact your doctor immediately.

Other Important Information

- Valproic acid oral solution, USP should be taken exactly as prescribed by your doctor to get the most benefit from your medication and reduce the risk of side effects.
- If you have taken more than the prescribed dose of valproic acid oral solution, USP, contact your hospital emergency room or local poison center immediately.
- Valproic acid oral solution, USP was prescribed for your particular condition. Do not use it for another condition or give the drug to others.

Facts About Birth Defects

It is important to know that birth defects may occur even in children of individuals not taking any medications or without any additional risk factors.

This summary provides important information about the use of valproic acid oral solution, USP to women who could become pregnant. If you would like more information about the other potential risks and benefits of valproic acid oral solution, USP, ask your doctor or pharmacist to let you read the professional labeling and then discuss it with them. If you have any questions or concerns about taking valproic acid oral solution, USP, you should discuss them with your doctor.

Call your doctor for medical advice about side effects. You may report side effects to Hi-Tech Pharmacal Co., Inc. at 1-800-262-9010 or FDA at 1-800-FDA-1088.

DISTRIBUTED BY:

ATLANTIC BIOLOGICALS CORP.

MIAMI, FL 33179

Medication Guide

Valproic Acid Oral Solution, USP

(val • pro • ic acid)

Revised 06/2022

Read this Medication Guide before you start taking Valproic Acid Oral Solution, USP and each time you get a refill. There may be new information. This information does not take the place of talking to your healthcare provider about your medical condition or treatment.

What is the most important information I should know about Valproic Acid Oral Solution, USP?

Do not stop taking Valproic Acid Oral Solution, USP without first talking to your healthcare provider.

Stopping Valproic Acid Oral Solution, USP suddenly can cause serious problems.

Valproic Acid Oral Solution, USP can cause serious side effects, including:

1.Serious liver damage that can cause death, especially in children younger than 2 years old.The risk of getting this serious liver damage is more likely to happen within the first 6 months of treatment.

Call your healthcare provider right away if you get any of thefollowing symptoms:

•nausea or vomiting that does not go away•loss of appetite•pain on the right side of your stomach (abdomen)•dark urine•swelling of your face•yellowing of your skin or the whites of your eyes

In some cases, liver damage may continue despite stopping the drug.

1.Valproic Acid Oral Solution, USP may harm your unborn baby.2.If you take Valproic Acid Oral Solution, USP during pregnancy for any medical condition, your baby is at risk for serious birth defects that affect the brain and spinal cord and are called spina bifida or neural tube defects. These defects occur in 1 to 2 out of every 100 babies born to mothers who use this medicine during pregnancy. These defects can begin in the first month, even before you know you are pregnant. Other birth defects that affect the structures of the heart, head, arms, legs, and the opening where the urine comes out (urethra) on the bottom of the penis can also happen. Decreased hearing or hearing loss can also happen.3.Birth defects may occur even in children born to women who are not taking any medicines and do not have other risk factors.4.Taking folic acid supplements before getting pregnant and during early pregnancy can lower the chance of having a baby with a neural tube defect.5.If you take Valproic Acid Oral Solution, USP during pregnancy for any medical condition, your child is at risk for having a lower IQ and may be at risk for developing autism or attention deficit/hyperactivity disorder.6.There may be other medicines to treat your condition that have a lower chance of causing birth defects, decreased IQ, or other disorders in your child.7.Women who are pregnant must not take Valproic Acid Oral Solution, USP to prevent migraine headaches.8.All women of childbearing age (including girls from the start of puberty) should talk to their healthcare provider about using other possible treatments instead of Valproic Acid Oral Solution, USP. If the decision is made to use Valproic Acid Oral Solution, USP, you should use effective birth control (contraception).9.Tell your healthcare provider right away if you become pregnant while taking Valproic Acid Oral Solution, USP. You and your healthcare provider should decide if you will continue to take Valproic Acid Oral Solution, USP while you are pregnant.10.Pregnancy Registry: If you become pregnant while taking Valproic Acid Oral Solution, USP, talk to your healthcare provider about registering with the North American Antiepileptic Drug Pregnancy Registry. You can enroll in this registry by calling toll-free 1-888-233-2334 or by visiting the website, http://www.aedpregnancyregistry.org/. The purpose of this registry is to collect information about the safety of antiepileptic drugs during pregnancy.11.Inflammation of your pancreas that can cause death.

Call your healthcare provider right away if you have any of these symptoms:

•severe stomach pain that you may also feel in your back•nausea or vomiting that does not go away•Like other antiepileptic drugs, Valproic Acid Oral Solution, USP, may cause suicidal thoughts or actions in avery small number of people, about 1 in 500.

Call a healthcare provider right away if you have any of these symptoms, especially if they are new, worse, or worry you:

•thoughts about suicide or dying•attempts to commit suicide•new or worse depression•new or worse anxiety•feeling agitated or restless•panic attacks•trouble sleeping (insomnia)•new or worse irritability•acting aggressive, being angry, or violent•acting on dangerous impulses•an extreme increase in activity and talking (mania)•other unusual changes in behavior or mood

How can I watch for early symptoms of suicidal thoughts and actions?

•Pay attention to any changes, especially sudden changes in mood, behaviors, thoughts, or feelings.•Keep all follow-up visits with your healthcare provider as scheduled.

Call your healthcare provider between visits as needed, especially if you are worried about symptoms.

Do not stop Valproic Acid Oral Solution, USP without first talking to a healthcare provider. Stopping Valproic Acid Oral Solution, USP suddenly can cause serious problems. Stopping a seizure medicine suddenly in a patient who has epilepsy can cause seizures that do not stop (status epilepticus).

Suicidal thoughts or actions can be caused by things other than medicines. If you have suicidal thoughts or actions, your healthcare provider may check for other causes.

What is Valproic Acid Oral Solution, USP?

Valproic Acid Oral Solution, USP is prescription medicines used alone or with other medicines, to treat:

•complex partial seizures in adults and children 10 years of age and older•simple and complex absence seizures, with or without other seizure types

Who should not take Valproic Acid Oral Solution, USP?

Do not take Valproic Acid Oral Solution, USP if you:

•have liver problems•have or think you have a genetic liver problem caused by a mitochondrial disorder (e.g. Alpers-Huttenlocher syndrome)•are allergic to divalproex sodium, valproic acid, sodium valproate, or any of the ingredients in Valproic Acid Oral Solution, USP. See the end of this leaflet for a complete list of ingredients in Valproic Acid Oral Solution, USP.•have a genetic problem called urea cycle disorder•are taking it to prevent migraine headaches and are either pregnant or may become pregnant because you are not using effective birth control (contraception)

What should I tell my healthcare provider before taking Valproic Acid Oral Solution, USP?

Before you take Valproic Acid Oral Solution, USP, tell your healthcare provider if you:

•have a genetic liver problem caused by a mitochondrial disorder (e.g. Alpers-Huttenlocher syndrome)•drink alcohol•are pregnant or breastfeeding. Valproic Acid Oral Solution, USP can pass into breast milk. Talk to your healthcare provider about the best way to feed your baby if you take Valproic Acid Oral Solution, USP•have or have had depression, mood problems, or suicidal thoughts or behavior•have any other medical conditions

Tell your healthcare provider about all the medicines you take, including prescription and non-prescription medicines, vitamins, herbal supplements and medicines that you take for a short period of time.

Taking Valproic Acid Oral Solution, USP with certain other medicines can cause side effects or affect how well they work. Do not start or stop other medicines without talking to your healthcare provider.

Know the medicines you take. Keep a list of them and show it to your healthcare provider and pharmacist each time you get a new medicine.

How should I take Valproic Acid Oral Solution, USP?

•Take Valproic Acid Oral Solution, USP exactly as your healthcare provider tells you. Your healthcare provider will tell you how much Valproic Acid Oral Solution, USP to take and when to take it.•Your healthcare provider may change your dose.•Do not change your dose of Valproic Acid Oral Solution, USP without talking to your healthcare provider.•Do not stop taking Valproic Acid Oral Solution, USP without first talking to your healthcare provider.Stopping Valproic Acid Oral Solution, USP suddenly can cause serious problems.•If you take too much Valproic Acid Oral Solution, USP, call your healthcare provider or local Poison Control Center right away.

What should I avoid while taking Valproic Acid Oral Solution, USP?

•Valproic Acid Oral Solution, USP can cause drowsiness and dizziness. Do not drink alcohol or take other medicines that make you sleepy or dizzy while taking Valproic Acid Oral Solution, USP, until you talk with your doctor. Taking Valproic Acid Oral Solution, USP with alcohol or drugs that cause sleepiness or dizziness may make your sleepiness or dizziness worse.•Do not drive a car or operate dangerous machinery until you know how Valproic Acid Oral Solution, USP affects you. Valproic Acid Oral Solution, USP can slow your thinking and motor skills.

What are the possible side effects of Valproic Acid Oral Solution, USP?

•See “What is the most important information I should know about Valproic Acid Oral Solution, USP?”

Valproic Acid Oral Solution, USP can cause other serious side effects including:

•Bleeding problems: red or purple spots on your skin, bruising, pain and swelling into your joints due to bleeding or bleeding from your mouth or nose.•High ammonia levels in your blood: feeling tired, vomiting, changes in mental status.•Low body temperature (hypothermia): drop in your body temperature to less than 95°F, feeling tired, confusion, coma.•Allergic (hypersensitivity) reactions: fever, skin rash, hives, sores in your mouth, skin blistering and peeling of your skin, swelling of your lymph nodes, swelling of your face, eyes, lips, tongue, or throat, trouble swallowing or breathing.•Drowsiness or sleepiness in the elderly.This extreme drowsiness may cause you to eat or drink less than you normally would. Tell your doctor if you are not able to eat or drink as you normally do. Your doctor may start you at a lower dose of Valproic Acid Oral Solution, USP.

Call your healthcare provider right away, if you have any of the symptoms listed above.

The common side effects of Valproic Acid Oral Solution, USP include:

•nausea•headache•sleepiness•vomiting•weakness•tremor•dizziness•stomach pain•blurry vision•double vision•diarrhea•increased appetite•weight gain•hair loss•loss of appetite•problems with walking or coordinationThese are not all of the possible side effects of Valproic Acid Oral Solution, USP. For more information, ask your healthcare provider or pharmacist.Tell your healthcare provider if you have any side effect that bothers you or that does not go away.Call your doctor for medical advice about side effects. You may report side effects to Akorn Operating Company LLC at 1-800-932-5676 or FDA at 1-800-FDA-1088.How should I store Valproic Acid Oral Solution, USP?Store Valproic Acid Oral Solution, USP below 86°F (30°C).Keep Valproic Acid Oral Solution, USP and all medicines out of the reach of children.General information about the safe and effective use of Valproic Acid Oral Solution, USPMedicines are sometimes prescribed for purposes other than those listed in a Medication Guide. Do not use Valproic Acid Oral Solution, USP for a condition for which it was not prescribed. Do not give Valproic Acid Oral Solution, USP to other people, even if they have the same symptoms that you have. It may harm them.This Medication Guide summarizes the most important information about Valproic Acid Oral Solution, USP. If you would like more information, talk with your healthcare provider. You can ask your pharmacist or healthcare provider for information about Valproic Acid Oral Solution, USP that is written for health professionals.What are the ingredients in Valproic Acid Oral Solution, USP?Active ingredient: valproic acidInactive ingredients: FD&C Red No. 40, methylparaben, natural and artificial raspberry flavor, propylparaben, purified water, sodium hydroxide, sorbitol, and sucrose.This Medication Guide has been approved by the U.S. Food and Drug Administration.Dispense the accompanying Medication Guide to each patient.Distributed by:Akorn Operating Company LLCGurnee, ILRevised 06/2022